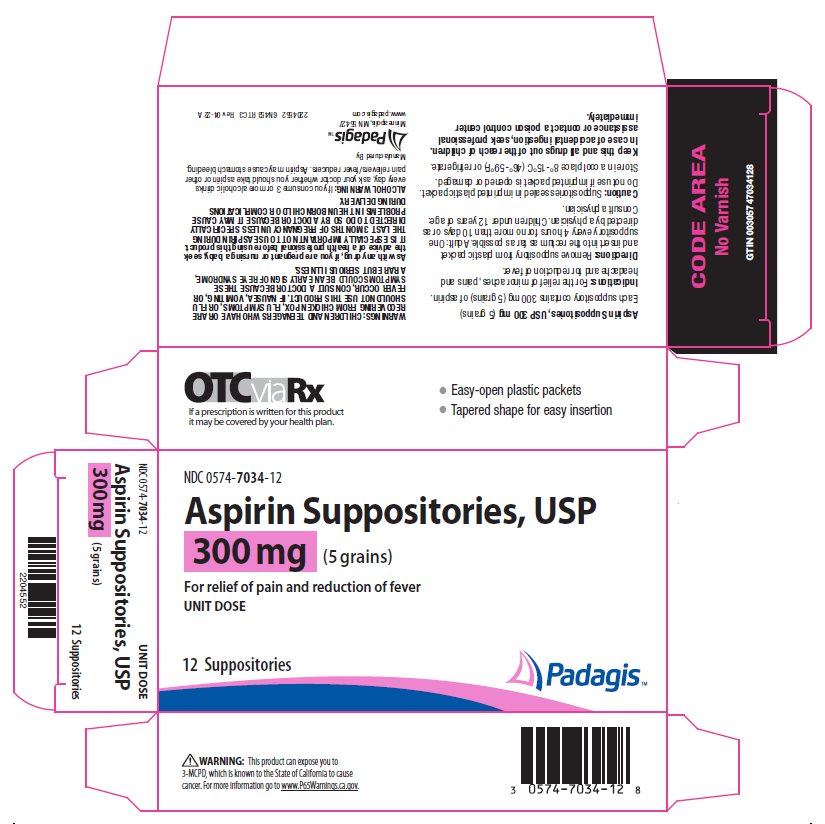 DRUG LABEL: aspirin
NDC: 0574-7034 | Form: SUPPOSITORY
Manufacturer: Padagis US LLC
Category: otc | Type: HUMAN OTC DRUG LABEL
Date: 20220430

ACTIVE INGREDIENTS: ASPIRIN 300 mg/1 1
INACTIVE INGREDIENTS: HYDROGENATED PALM KERNEL OIL; SILICON DIOXIDE

Aspirin Suppositories, USP

Active ingredient

Aspirin Suppositories, USP 300 mg (5 grains)

Each suppository contains 300 mg (5 grains) of aspirin.

Indications:

For the relief of minor aches, pains and headache and for reduction of fever.

Directions

Remove suppository from plastic packet and insert into the rectum as far as possible. Adult: One suppository every 4 hours for no more than 10 days or as directed by a physician. Children under 12 years of age: Consult a physician.

Caution:

Suppositories sealed in imprinted plastic packet. Do not use if imprinted packet is opened or damaged.

Store in a cool place 8° - 15°C (46° - 59°F) or refrigerate.

Keep this and all drugs out of the reach of children.

In case of accidental ingestion, seek professional assistance or contact a poison control center immediately.

Warnings

CHILDREN AND TEENAGERS WHO HAVE OR ARE RECOVERING FROM CHICKEN POX, FLU SYMPTOMS, OR FLU SHOULD NOT USE THIS PRODUCT. IF NAUSEA, VOMITING, OR FEVER OCCUR, CONSULT A DOCTOR BECAUSE THESE SYMPTOMS COULD BE AN EARLY SIGN OF REYE SYNDROME, A RARE BUT SERIOUS ILLNESS.

As with any drug, if you are pregnant or nursing a baby, seek the advice of a health professional before using this product. IT IS ESPECIALLY IMPORTANT NOT TO USE ASPIRIN DURING THE LAST 3 MONTHS OF PREGNANCY UNLESS SPECIFICALLY DIRECTED TO DO SO BY A DOCTOR BECAUSE IT MAY CAUSE PROBLEMS IN THE UNBORN CHILD OR COMPLICATIONS DURING DELIVERY.

ALCOHOL WARNING:

If you consume 3 or more alcoholic drinks every day, ask your doctor whether you should take aspirin or other pain relievers/fever reducers. Aspirin may cause stomach bleeding.

Manufactured by Padagis

Minneapolis, MN 55427

Rev 04-22

Package/Label Principal Display Panel – 300 mg

NDC 0574-7034-12

Aspirin Suppositories, USP

300 mg (5 grains)

For relief of pain and reduction of fever

UNIT DOSE

12 Suppositories